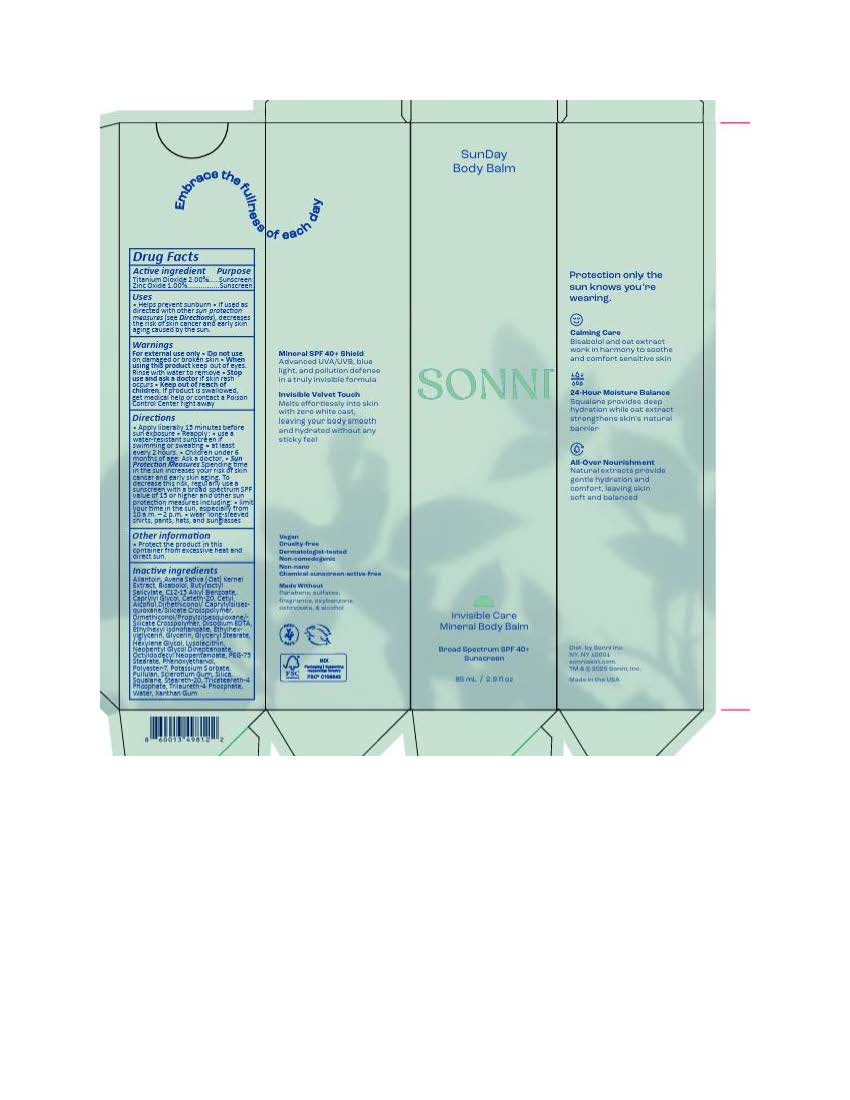 DRUG LABEL: Sonni SunDay Body Balm
NDC: 85260-492 | Form: LOTION
Manufacturer: Sonni
Category: otc | Type: HUMAN OTC DRUG LABEL
Date: 20251021

ACTIVE INGREDIENTS: TITANIUM DIOXIDE 22 mg/1 mL; ZINC OXIDE 11 mg/1 mL
INACTIVE INGREDIENTS: STEARETH-20; .ALPHA.-BISABOLOL, (+)-; ALLANTOIN; CETYL ALCOHOL; PULLULAN; CAPRYLYL GLYCOL; HEXYLENE GLYCOL; POTASSIUM SORBATE; NEOPENTYL GLYCOL DIHEPTANOATE; PHENOXYETHANOL; SILICON DIOXIDE; AVENA SATIVA WHOLE; POLYESTER-7; BUTYLOCTYL SALICYLATE; GLYCERIN; WATER; TRICETEARETH-4 PHOSPHATE; XANTHAN GUM; ETHYLHEXYLGLYCERIN; TRILAURETH-4 PHOSPHATE; C12-20 ALKYL BENZOATE; OCTYLDODECYL NEOPENTANOATE; ETHYLHEXYL ISONONANOATE; SQUALANE; DIMETHICONOL/PROPYLSILSESQUIOXANE/SILICATE CROSSPOLYMER (450000000 MW)

Sonni SunDay Body Balm